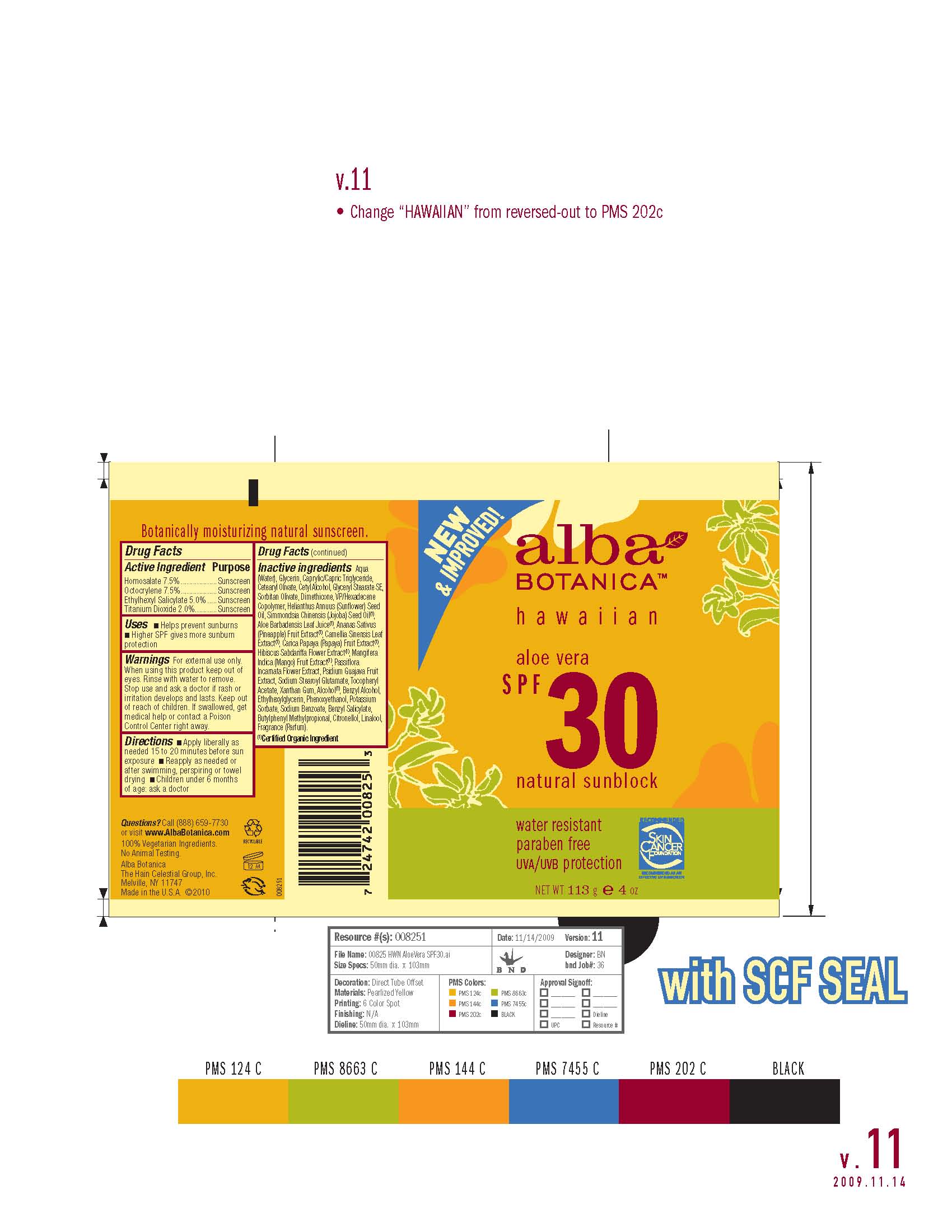 DRUG LABEL: Alba Hawaiian Aloe Vera Sunblock SPF 30
NDC: 61995-2825 | Form: CREAM
Manufacturer: The Hain Celestial Group, Inc.
Category: otc | Type: HUMAN OTC DRUG LABEL
Date: 20100714

ACTIVE INGREDIENTS: Homosalate 7.5 g/100 g; Octocrylene 7.5 g/100 g; Octisalate 5.0 g/100 g; Titanium Dioxide 2.0 g/100 g

Drug Facts

ACTIVE INGREDIENTS

Homosalate 7.5%

Octocrylene 7.5%

Ethylhexyl Salicilate 5.0%

Titanium Dioxide 2.0%

USES

- Helps prevent sunburns
- Higher SPF gives more sunburn protection

- Apply liberally as needed 15 to 20 minutes before sun exposure

- Reapply as needed or after swimming, perspiring or towel drying

- Children under 6 months of age: ask doctor

WARNINGS

For external use only. When using this product keep out of eyes. Rinse with water to remove. Stop use and ask a doctor if rash or irritation develops and lasts. Keep out of reach of children. If swallowed, get medical help or contact Poison Center right away.

QUESTIONS?

Call (888) 659-7730 or visit www.AlbaBotanica.com

100% Vegetarian Ingredients

No Animal Testing

Alba Botanica

The Hain Celestial Group, Inc.

Melville, NY 11747

Made in the U.S.A.